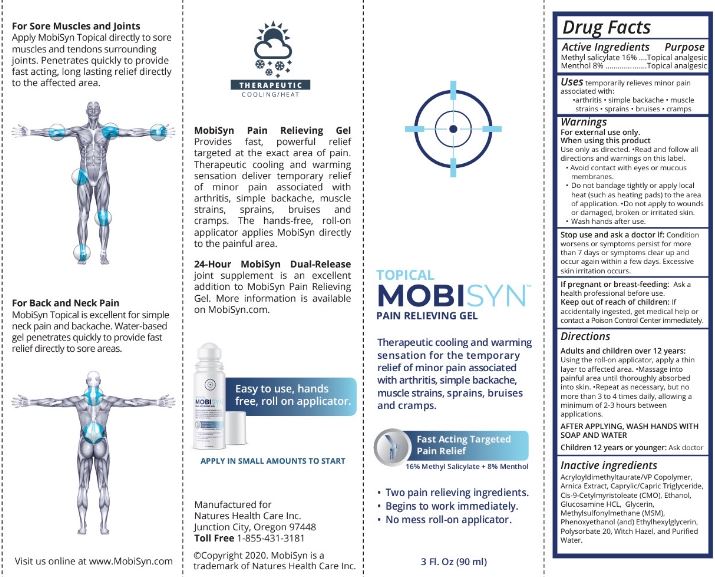 DRUG LABEL: Mobisyn Pain Relieving
NDC: 73799-001 | Form: GEL
Manufacturer: Chrono Health Care dba Natures Health Care
Category: otc | Type: HUMAN OTC DRUG LABEL
Date: 20200516

ACTIVE INGREDIENTS: METHYL SALICYLATE 16 mg/100 mL; MENTHOL, UNSPECIFIED FORM 8 mg/100 mL
INACTIVE INGREDIENTS: AMMONIUM ACRYLOYLDIMETHYLTAURATE/VP COPOLYMER; GLUCOSAMINE HYDROCHLORIDE; MEDIUM-CHAIN TRIGLYCERIDES; GLYCERIN; PHENOXYETHANOL; ALCOHOL; WATER; DIMETHYL SULFONE; ETHYLHEXYLGLYCERIN; POLYSORBATE 20; WITCH HAZEL; CETYL MYRISTOLEATE

Mobisyn Pain Relieving Gel

Active Ingredients

Methyl salicylate 16%

Menthol 8%

Purpose

Topical analgesic

Uses

temporarily relieves minor pain associated with:

- arthritis
- simple backache
- muscle strains
- sprains
- bruises
- cramps

Warnings

For external use only.

When using this product

Use only as directed. •Read and follow all directions and warnings on this label.

- Avoid contact with eyes or mucous membranes.
- Do not bandage tightly or apply local heat (such as heating pads) to the area of application. •Do not apply to wounds or damaged, broken or irritated skin.
- Wash hands after use.

Stop use and ask a doctor if:

Condition worsens or syptoms persist for more than 7 days or symptoms clear up and occur again with a few days. Excessive skin irritation occurs.

If pregnant or breast-feeding:

Ask a health professional before use.

Keep out of reach of children:

If accidentally ingested, get medical help or contact a Poison Control Center immediately.

Directions

Adults and children over 12 years:

Using the roll-on applicator, apply a thin layer to affected area. •Massage into painful area until thoroughly absorbed into skin. •Repeat as necessay, but no more than 3 to 4 times daily, allowing a minimum of 2-3 hours between applications.

AFTER APPLYING, WASH HANDS WITH SOAP AND WATER

Children 12 years or younger: Ask doctor

Inactive ingredients

Acryloyldimethyltaurate/VP Copolymer, Arnica Extract, Caprylic/Capric Triglyceride, Cis-9-Cetylmyristoleate (CMO), Ethanol, Glucosamine HCL, Glycerin, Methylsulfonylmethane (MSM), Phenoxyethanol (and) Ethylhexylglycerin, Polysorbate 20, Witch Hazel, and Purified Water.